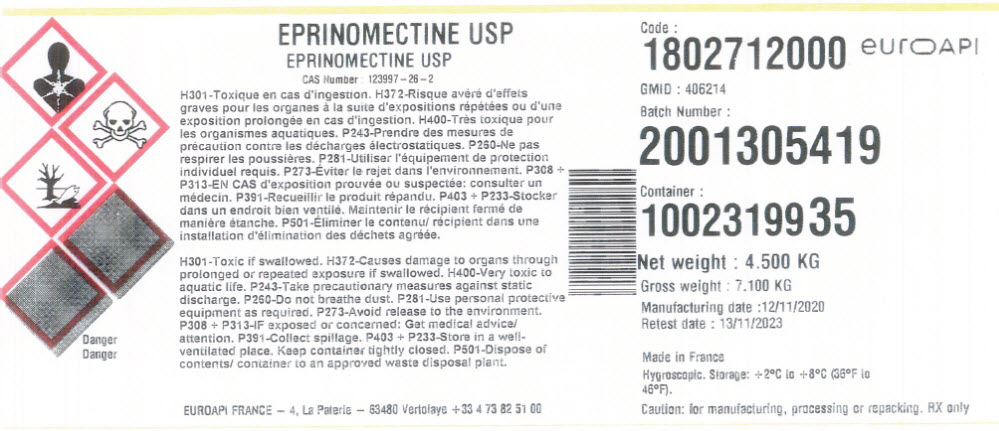 DRUG LABEL: Eprinomectine
NDC: 82298-125 | Form: POWDER
Manufacturer: EUROAPI France
Category: other | Type: BULK INGREDIENT - ANIMAL DRUG
Date: 20220317

ACTIVE INGREDIENTS: EPRINOMECTIN 1 kg/1 kg

EPRINOMECTINE USP

PRINCIPAL DISPLAY PANEL - Shipping Label

EPRINOMECTINE USP
CAS Number : 123997 – 26 – 2

H301-Toxic if swallowed. H372-Causes damage to organs through
prolonged or repeated exposure if swallowed. H400-Very toxic to
aquatic life. P243-Take precautionary measures against static
discharge. P260-Do not breathe dust. P281-Use personal protective
equipment as required. P273-Avoid release to the environment.
P308 + P313-IF exposed or concerned: Get medical advice/
attention. P391-Collect spillage. P403 + P233-Store in a well-
ventilated place. Keep container tightly closed. P501-Dispose of
contents/ container to an approved waste disposal plant.

Danger

EUROAPI FRANCE – 4, La Paterie – 63480 Vertolaye +33 4 73 82 51 00

Code :
1802712000 eurOAPI
GMID : 406214
Batch Number :
2001305419
Container :
1002319935

Net weight : 4.500 KG
Gross weight : 7.100 KG
Manufacturing date :12/11/2020
Retest date : 13/11/2023

Made in France
Hygroscopic. Storage: +2°C to +8°C (36°F to
46°F).

Caution: for manufacturing, processing or repacking. RX only